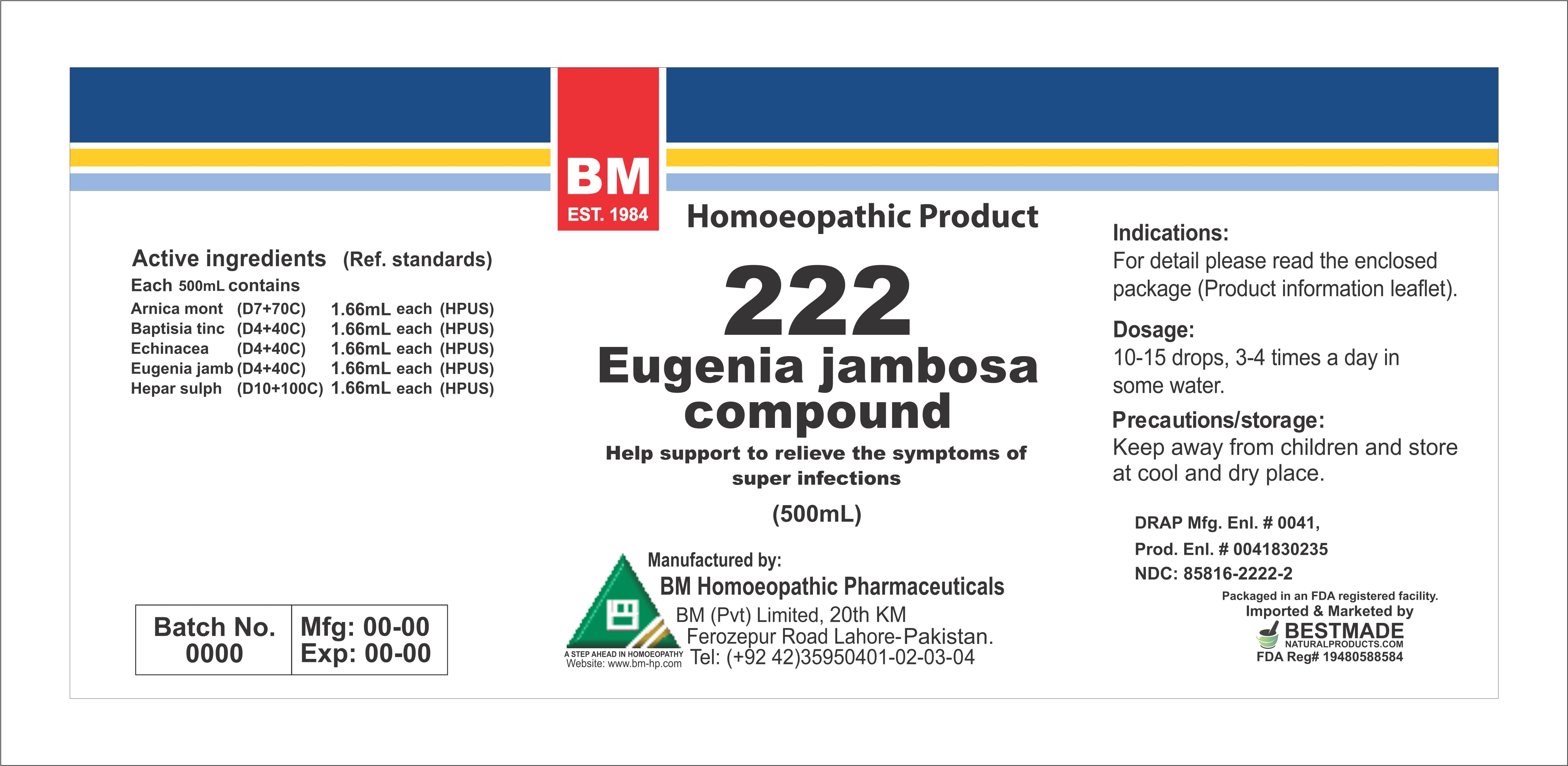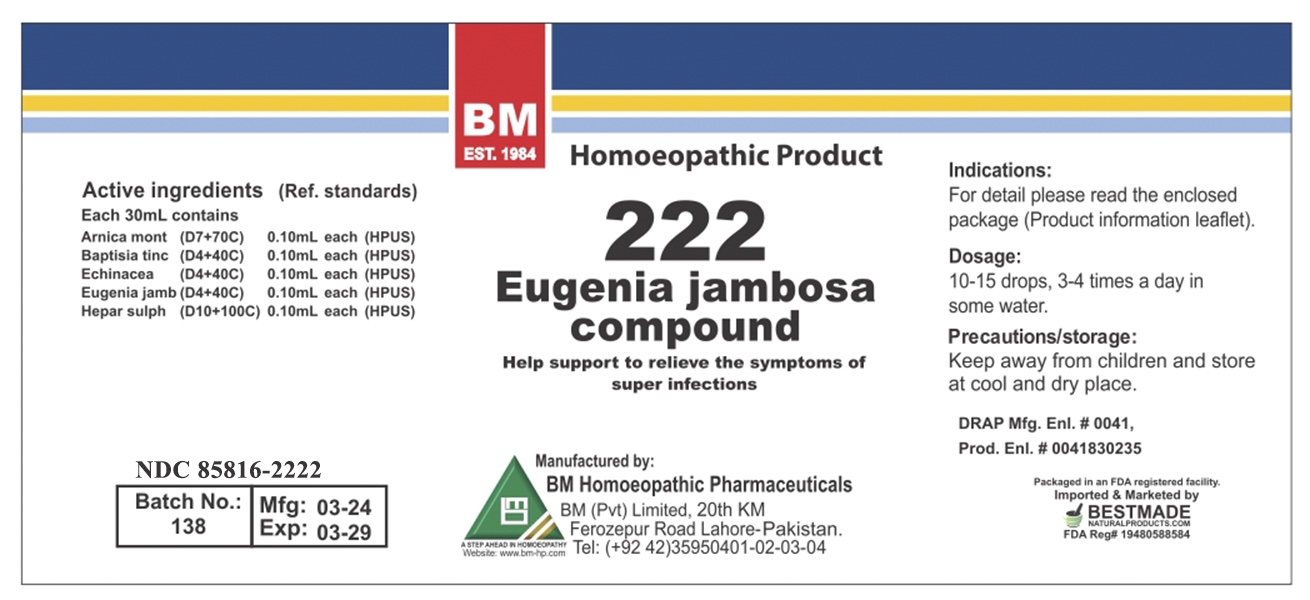 DRUG LABEL: EUGENIA JAMBOSA
NDC: 85816-2222 | Form: LIQUID
Manufacturer: BM Private Limited
Category: homeopathic | Type: HUMAN OTC DRUG LABEL
Date: 20260215

ACTIVE INGREDIENTS: SYZYGIUM JAMBOS SEED 4 [hp_X]/1 mL; ARNICA MONTANA 7 [hp_X]/1 mL; CALCIUM SULFIDE 10 [hp_X]/1 mL; BAPTISIA TINCTORIA ROOT 4 [hp_X]/1 mL; ECHINACEA, UNSPECIFIED 4 [hp_X]/1 mL
INACTIVE INGREDIENTS: ALCOHOL 0.96 mL/1 mL

HOMEOPATHIC LIQUID EUGENIA JAMBOSA/ BM222

DOSAGE AND ADMINISTRATION

10-15 drops, 3-4 times a day in some water

ACTIVE INGREDIENT

Arnica montana, baptisia, echinacea, eugenia jambosa, hepar shulph

INACTIVE INGREDIENT

ALCOHOL

INDICATIONS AND USAGE

For detail, please read the enclosed package (product information leaflet)

PURPOSE

For detail, please read the enclosed package (product information leaflet)

KEEP OUT OF REACH OF CHILDREN

Precautions/storage:
Keep away from children and store at cool and dry place.

WARNINGS

Precautions/storage:
Keep away from children and store at cool and dry place.

Package 1:

Package 2: